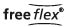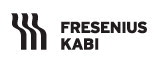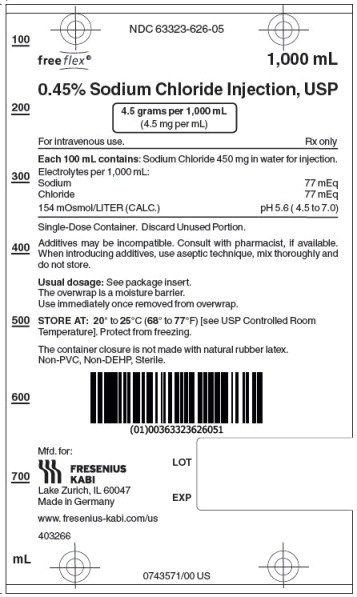 DRUG LABEL: Sodium chloride
NDC: 63323-626 | Form: INJECTION, SOLUTION
Manufacturer: Fresenius Kabi USA, LLC
Category: prescription | Type: HUMAN PRESCRIPTION DRUG LABEL
Date: 20240722

ACTIVE INGREDIENTS: SODIUM CHLORIDE 450 mg/100 mL
INACTIVE INGREDIENTS: WATER

0.45% Sodium Chloride Injection, USP

Rx only

DESCRIPTION:

0.45% Sodium Chloride Injection, USP solution is a sterile and nonpyrogenic solution intended for intravenous administration.

Each 100 mL of 0.45% Sodium Chloride Injection, USP contains 450 mg sodium chloride in water for injection. Electrolytes per 1,000 mL: sodium 77 mEq; chloride 77 mEq. The osmolarity is 154 mOsmol/L (calc.).

The pH in the 100 mL and smaller containers is 6.0; for the 250 mL and larger containers, the pH is 5.6. The pH range is 4.5 to 7.0 for all containers.

The solution contains no bacteriostat, antimicrobial agent or added buffer and is intended only as a single-dose injection. When smaller doses are required the unused portion should be discarded.

0.45% Sodium Chloride Injection, USP is a parenteral fluid and electrolyte replenisher.

Sodium chloride, USP is chemically designated NaCl, a white crystalline powder freely soluble in water.

Water for Injection, USP is chemically designated H2O.

The flexible plastic container is fabricated from a specially formulated non-plasticized, film containing polypropylene and thermoplastic elastomers (freeflex® bag). The amount of water that can permeate from the container into the overwrap is insufficient to affect the solution significantly. Solutions in contact with the flexible container can leach out certain of the container's chemical components in very small amounts within the expiration period. The suitability of the container material has been confirmed by tests in animals according to USP biological tests for plastic containers.

CLINICAL PHARMACOLOGY:

When administered intravenously, these solutions provide a source of water and electrolytes.

Solutions which provide combinations of hypotonic or isotonic concentrations of sodium chloride are suitable for parenteral maintenance or replacement of water and electrolyte requirements.

Isotonic concentrations of sodium chloride are suitable for parenteral replacement of chloride losses that exceed or equal the sodium loss. Hypotonic concentrations of sodium chloride are suited for parenteral maintenance of water requirements when only small quantities of salt are desired. A hypertonic concentration of sodium chloride may be used to repair severe salt depletion syndrome.

Sodium chloride in water dissociates to provide sodium (Na ^+) and chloride (Cl ^−) ions. Sodium (Na ^+) is the principal cation of the extracellular fluid and plays a large part in the therapy of fluid and electrolyte disturbances. Chloride (Cl ^−) has an integral role in buffering action when oxygen and carbon dioxide exchange occurs in the red blood cells. The distribution and excretion of sodium (Na ^+) and chloride (Cl ^−) are largely under the control of the kidney which maintains a balance between intake and output.

Water is an essential constituent of all body tissues and accounts for approximately 70% of total body weight. Average normal adult daily requirements range from two to three liters (1.0 to 1.5 liters each for insensible water loss by perspiration and urine production).

Water balance is maintained by various regulatory mechanisms. Water distribution depends primarily on the concentration of electrolytes in the body compartments and sodium (Na ^+) plays a major role in maintaining physiologic equilibrium.

INDICATIONS AND USAGE:

Intravenous solutions containing sodium chloride are indicated for parenteral replenishment of fluid and sodium chloride as required by the clinical condition of the patient.

CONTRAINDICATIONS:

None known.

WARNINGS:

0.45% Sodium chloride injection should be used with great care, if at all, in patients with congestive heart failure, severe renal insufficiency and in clinical states in which there exists edema with sodium retention.

The intravenous administration of 0.45% Sodium chloride injection can cause fluid and/or solute overloading resulting in dilution of serum electrolyte concentrations, overhydration, congested states or pulmonary edema.

The risk of dilutive states is inversely proportional to the electrolyte concentration of the injections. The risk of solute overload causing congested states with peripheral and pulmonary edema is directly proportional to the electrolyte concentrations of the injections.

In patients with diminished renal function, administration of 0.45% Sodium chloride injection may result in sodium retention.

PRECAUTIONS:

General

Do not use plastic containers in series connections. Such use could result in air embolism due to residual air being drawn from the primary container before administration of the fluid from the secondary container is completed.

Pressurizing intravenous solutions contained in flexible plastic containers to increase flow rates can result in air embolism if the residual air in the container is not fully evacuated prior to administration.

Use of a vented intravenous administration set with the vent in the open position could result in air embolism. Vented intravenous administration sets with the vent in the open position should not be used with flexible plastic containers.

Laboratory Tests

Clinical evaluation and periodic laboratory determinations are necessary to monitor changes in fluid balance, electrolyte concentrations and acid-base balance during prolonged parenteral therapy or whenever the condition of the patient warrants such evaluation.

Drug Interactions

Caution must be exercised in the administration of 0.45% Sodium chloride injection to patients receiving corticosteroids or corticotropin.

Carcinogenesis, Mutagenesis, Impairment of Fertility

Studies have not been performed with 0.45% Sodium chloride injection to evaluate the potential for carcinogenesis, mutagenesis or impairment of fertility.

Pregnancy

Teratogenic Effects

Pregnancy Category C

Animal reproduction studies have not been conducted with 0.45% Sodium chloride injection. It is also not known whether 0.45% Sodium chloride injection can cause fetal harm when administered to a pregnant woman or can affect reproduction capacity. 0.45% Sodium chloride injection should be given to a pregnant woman only if clearly needed.

Labor and Delivery

Studies have not been conducted to evaluate the effects of 0.45% Sodium chloride injection on labor and delivery. Caution should be exercised when administering this drug during labor and delivery.

Nursing Mothers

It is not known whether this drug is excreted in human milk. Because many drugs are excreted in human milk, caution should be exercised when 0.45% Sodium chloride injection is administered to a nursing mother.

Pediatric Use

The use of 0.45% Sodium chloride injection in pediatric patients is based on clinical practice.

Plasma electrolyte concentrations should be closely monitored in the pediatric population as this population may have impaired ability to regulate fluids and electrolytes.

The infusion of hypotonic fluids (0.45% Sodium chloride injection) together with the non-osmotic secretion of ADH may result in hyponatremia in patients with acute volume depletion. Hyponatremia can lead to headache, nausea, seizures, lethargy, coma, cerebral edema and death, therefore acute symptomatic hyponatremic encephalopathy is considered a medical emergency.

Geriatric Use

Clinical studies of 0.45% Sodium chloride injection did not include sufficient numbers of subjects aged 65 and over to determine whether they respond differently from younger subjects. Other reported clinical experience has not identified differences in responses between elderly and younger patients. In general, dose selection for an elderly patient should be cautious, usually starting at the low end of the dosing range, reflecting the greater frequency of decreased hepatic, renal, or cardiac function, and of concomitant disease or drug therapy.

This drug is known to be substantially excreted by the kidney, and the risk of toxic reactions to this drug may be greater in patients with impaired renal function. Because elderly patients are more likely to have decreased renal function, care should be taken in dose selection, and it may be useful to monitor renal function.

Do not administer unless solution is clear and container is undamaged. Discard unused portion.

ADVERSE REACTIONS:

Reactions which may occur because of the solution or the technique of administration include febrile response, infection at the site of injection, venous thrombosis or phlebitis extending from the site of injection, extravasation and hypervolemia.

If an adverse reaction does occur, discontinue the infusion, evaluate the patient, institute appropriate therapeutic countermeasures and save the remainder of the fluid for examination if deemed necessary.

In addition to the above listed adverse reactions hyponatremia has been reported for 0.45% Sodium chloride injection (see Pediatric Use).

OVERDOSAGE:

In the event of overhydration or solute overload, re-evaluate the patient and institute appropriate corrective measures (see WARNINGS, PRECAUTIONS, and ADVERSE REACTIONS).

DOSAGE AND ADMINISTRATION:

The dose is dependent upon the age, weight and clinical condition of the patient.

Additives may be incompatible. Consult with pharmacist, if available. When introducing additives, use aseptic technique, mix thoroughly and do not store.

Parenteral drug products should be inspected visually for particulate matter and discoloration prior to administration, whenever solution and container permit (see PRECAUTIONS).

INSTRUCTIONS FOR USE:

Check flexible container solution composition, lot number, and expiry date.

Do not remove solution container from its overwrap until immediately before use.

Use sterile equipment and aseptic technique.

Flexible Plastic Container (freeflex® bag)

To Open

1. Turn solution container over so that the text is face down. Using the pre-cut corner tabs, peel open the overwrap and remove solution container.
2. Check the solution container for leaks by squeezing firmly. If leaks are found, or if the seal is not intact, discard the solution.
3. Do not use if the solution is cloudy or a precipitate is present .

To Add Medication

1. Identify WHITE Additive Port with arrow pointing toward container.
2. Immediately before injecting additives, break off WHITE Additive Port Cap with the arrow pointing toward container.
3. Hold base of WHITE Additive Port horizontally.
4. Insert needle horizontally through the center of WHITE Additive Port’s septum and inject additives.
5. Mix container contents thoroughly.

Preparation for Administration

1. Immediately before inserting the infusion set, break off BLUE Infusion Port Cap with the arrow pointing away from container.
2. Use a non-vented infusion set or close the air-inlet on a vented set.
3. Close the roller clamp of the infusion set.
4. Hold the base of BLUE Infusion Port.
5. Insert spike through BLUE Infusion Port by rotating wrist slightly until the spike is inserted. NOTE: See full directions accompanying administration set.

WARNING: Do not use flexible container in series connections.

The flexible container is fabricated from a specially formulated non-plasticized, film containing polypropylene and thermoplastic elastomers (freeflex® bag). The amount of water that can permeate from the container into the overwrap is insufficient to affect the solution significantly. Solutions in contact with the flexible container can leach out certain of the container's chemical components in very small amounts within the expiration period. The suitability of the container material has been confirmed by tests in animals according to USP biological tests for plastic containers.

HOW SUPPLIED:

0.45% Sodium Chloride Injection, USP is supplied in single-dose flexible plastic containers as follows:

Product Code | Unit of Sale | Strength | Each
626050 | 63323-626-50 Package of 60 | 0.225 grams per 50 mL (4.5 mg per mL) | 63323-626-01 50 mL in a 100 mL freeflex® bag
626100 | 63323-626-00 Package of 50 | 0.45 grams per 100 mL (4.5 mg per mL) | 63323-626-02 100 mL in a 100 mL freeflex® bag
626250 | 63323-626-25 Package of 30 | 1.125 grams per 250 mL (4.5 mg per mL) | 63323-626-03 250 mL in a 250 mL freeflex® bag
626500 | 63323-626-55 Package of 20 | 2.25 grams per 500 mL (4.5 mg per mL) | 63323-626-04 500 mL in a 500 mL freeflex® bag
626010 | 63323-626-10 Package of 10 | 4.5 grams per 1,000 mL (4.5 mg per mL) | 63323-626-05 1,000 mL in a 1,000 mL freeflex® bag

STORE AT: 20° to 25°C (68° to 77°F) [see USP Controlled Room Temperature]. Protect from freezing.

The container closure is not made with natural rubber latex. Non-PVC, Non-DEHP, Sterile.

Manufactured for:

Lake Zurich, IL 60047
www.fresenius-kabi.com/us
Issued: September 2018

PACKAGE LABEL

PACKAGE LABEL - PRINCIPAL DISPLAY PANEL - Sodium Chloride 1,000 mL Bag Label

NDC 63323-626-05 1,000 mL

0.45% Sodium Chloride Injection, USP
4.5 grams per 1,000 mL (4.5 mg per mL)

For intravenous use.
Rx only